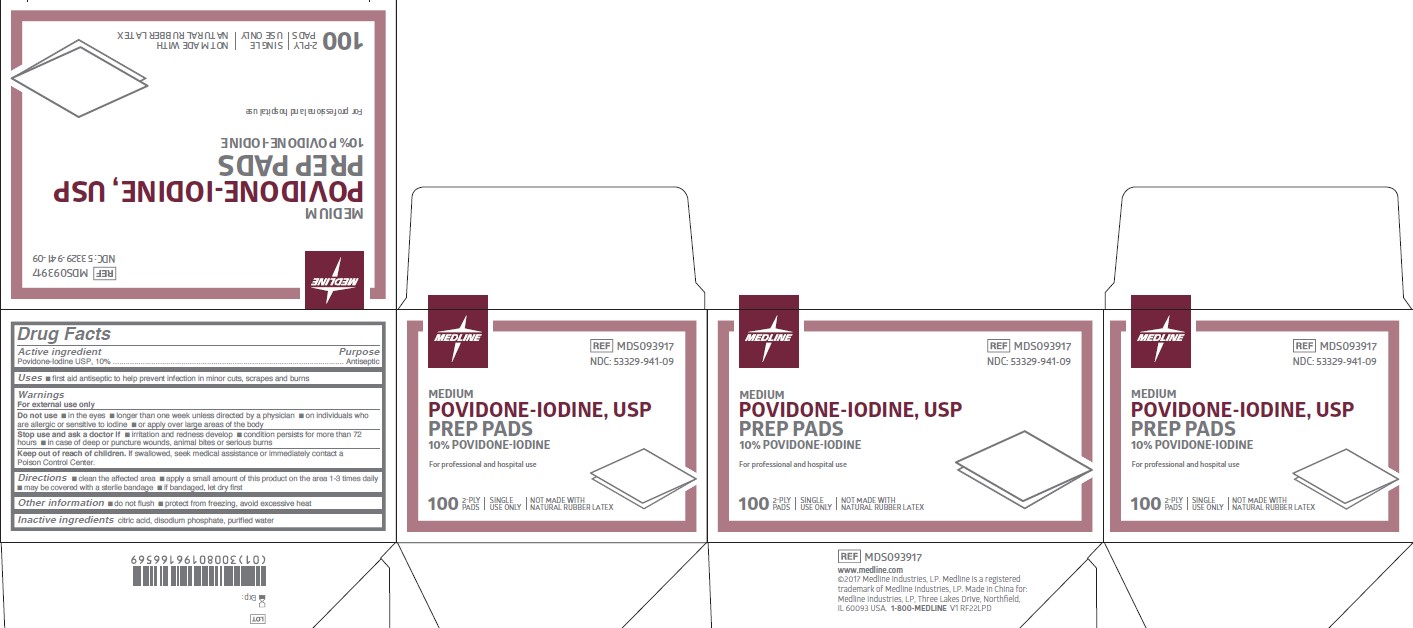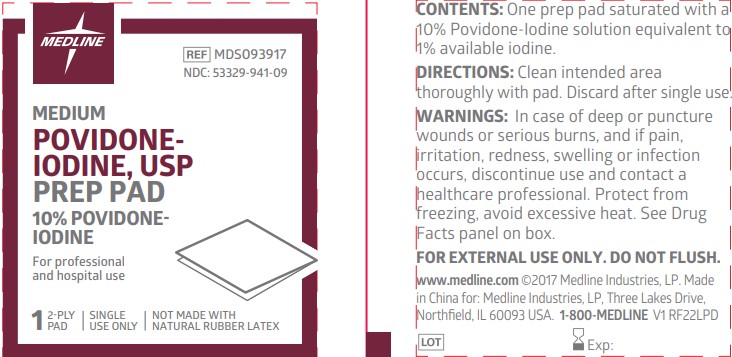 DRUG LABEL: Povidone-Iodine
NDC: 53329-941 | Form: CLOTH
Manufacturer: Medline Industries, LP
Category: otc | Type: HUMAN OTC DRUG LABEL
Date: 20251023

ACTIVE INGREDIENTS: POVIDONE-IODINE 10 mg/1 mL
INACTIVE INGREDIENTS: SODIUM PHOSPHATE, DIBASIC, ANHYDROUS; CITRIC ACID MONOHYDRATE; WATER

940-941 Povidone-Iodine Prep Pads

Active ingredient

Povidone-Iodine USP, 10%

Purpose

Antiseptic

Uses

- First aid antiseptic to help prevent infection in minor cuts, scrapes and burns

Warnings

For external use only.

Do not use

- in the eyes
- longer than 1 week unless directed by a physician
- on individuals who are allergic or sensitive to iodine
- or apply over large areas of the body

Stop use and ask a doctor if

- irritation and redness develop
- condition persists for more than 72 hours
- in case of deep or puncture wounds, animal bites or serious burns

Keep out of reach of children.

If swallowed, seek medical assistance or immediately contact a Poison Control Center.

Directions

- clean the affected area
- apply a small amount of this product on the area 1 to 3 times daily.
- may be covered with a sterile bandage
- if bandaged, let dry first

Other information

- do not flush
- protect from freezing, avoid excessive heat

Inactive ingredients

citric acid, disodium phosphate, purified water

Manufacturing Information

www.medline.com

©2017 Medline Industries, LP. Medline is a registered

trademark of Medline Industries, LP. Made in China for:

Medline Industries, LP, Three Lakes Drive, Northfield,

IL 60093 USA. 1-800-MEDLINE

REF: MDS093917